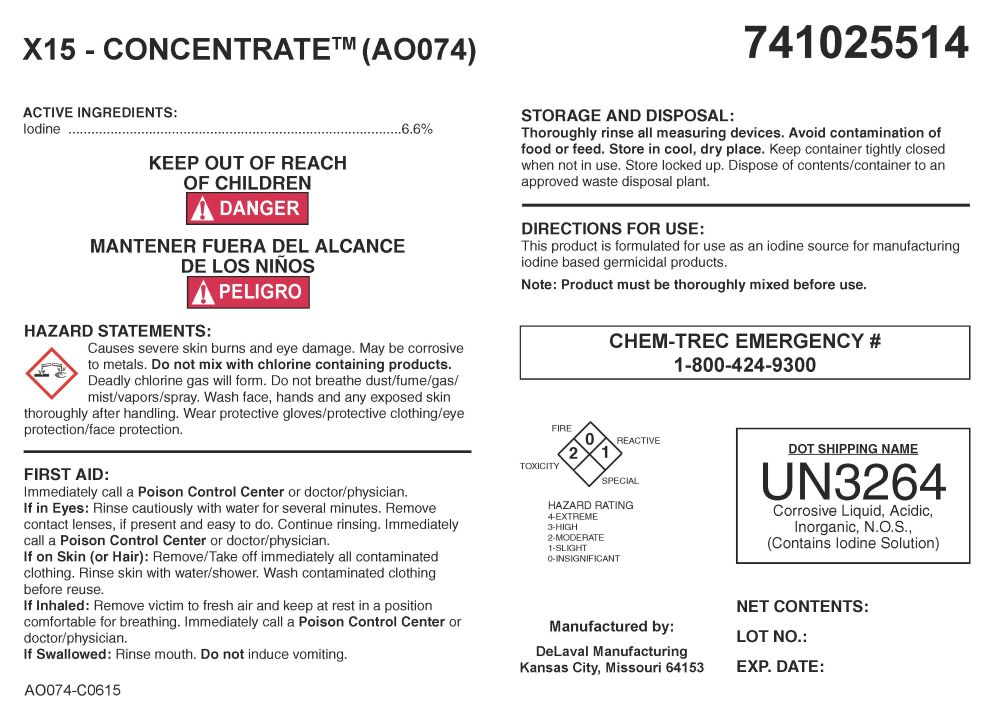 DRUG LABEL: X15 - Concentrate
NDC: 55756-787 | Form: SOLUTION
Manufacturer: DeLval, Inc
Category: other | Type: BULK INGREDIENT - ANIMAL DRUG
Date: 20260201

ACTIVE INGREDIENTS: IODINE 1 kg/1 kg
INACTIVE INGREDIENTS: WATER; SODIUM CHLORATE; SURFACTIN

X15 - Cocentrate (AO074)

KEEP OUT OF REACH OF CHILDREN! DANGER

-

HAZARD STATEMENTS:

Causes severe skin burns and eye damage. May be corrosive to metals. Do not mix with chlorine containing products. Deafly chlorine gas will form. Do not breathe dust/fumes/gas/mist/vapors/spray. Wash face, hands and any exposed skin thoroughly after handling. Wear protective gloves/protective clothing/eye protection/face protection.

FIRST AID:

Immediately call a Poison Control Center or doctor/physician.

If in Eyes: Rinse cautiously with water for several minutes. Remove contacts lenses, if present and easy to do, Continue rinsing. Immediately call a Poison Control Center or Doctor/physician.

If on Skin (or Hair): Remove/Take off immediately all contaminated clothing. Rinse skin with water/shower. Wash contaminated clothing before resue.

If Inhaled: Remove victim to fresh air and keep at rest in a position comfortable for breathing. Call a Poison Control Center or doctor/physician if you feel unwell.

If Swallowed: Rinse mouth. Do Not induce vomiting.

STORAGE AND DISPOSAL

Thoroughly rinse all measuring devices. Avoid contamination of food or feed. Store in cool, dry place. Keep container tightly closed when not in use. Store locked up. Dispose of contents/container to an approved waste disposal plant.

Directions for Use

This product is formulated for use as an iodine source for manufacturing iodine based germicidal products.

Note: Product must be thoroughly mixed before use.

FOR ADDITIONAL INFORMATION CONSULT THE SAFETY DATA SHEET

CHEMTREC EMERGENCY # 1-800-424-9300

DOT SHIPPING NAME

UN3264

Corrosive liquid, Acidic Inorganic, N.O.S.

(Contains Iodine Solution)

HOW SUPPLIED

Manufactured by:

DeLaval Manufacuturing

Kansas City, MO 64153